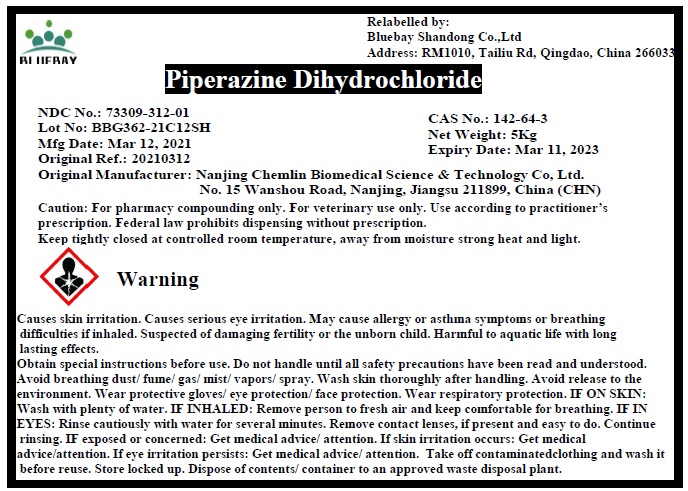 DRUG LABEL: Piperazine Dihydrochloride
NDC: 73309-312 | Form: POWDER
Manufacturer: BLUEBAY SHANDONG CO.,LTD
Category: other | Type: BULK INGREDIENT
Date: 20210708

ACTIVE INGREDIENTS: PIPERAZINE DIHYDROCHLORIDE 1 kg/1 kg

Piperazine Dihydrochloride